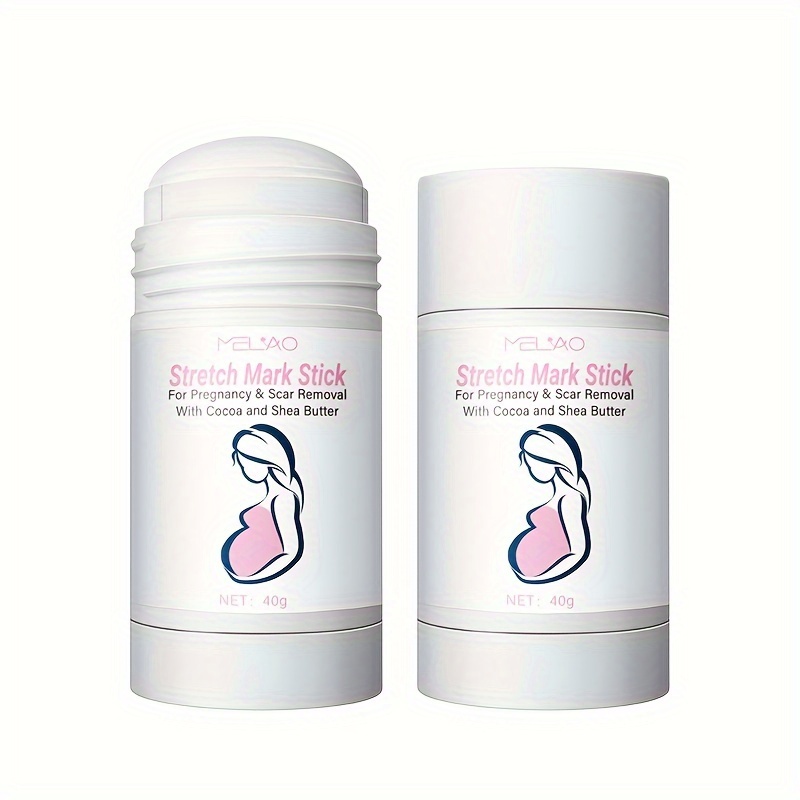 DRUG LABEL: MELAO Stretch Mark Stick
NDC: 83566-578 | Form: STICK
Manufacturer: Guangzhou Yilong Cosmetics Co., Ltd
Category: otc | Type: HUMAN OTC DRUG LABEL
Date: 20240810

ACTIVE INGREDIENTS: 3,5-DIBROMOSALICYLIC ACID 4 g/100 g
INACTIVE INGREDIENTS: LIMNANTHES ALBA WHOLE 2 g/100 g; WATER 60 g/100 g; PEG-9 DIGLYCIDYL ETHER/SODIUM HYALURONATE CROSSPOLYMER 2 g/100 g; ASCORBIC ACID 8 g/100 g; SIMMONDSIA CHINENSIS SEED 2 g/100 g; GLYCERIN 3 g/100 g; ASCORBYL GLUCOSIDE 15 g/100 g; 3-O-ETHYL ASCORBIC ACID 4 g/100 g

Active ingredients

Salicylic Acid 4%

Inactive ingredients

Water 60%

Ascorbyl Glucoside 15%

Ascorbic Acid 8%

3-0-Ethyl Ascorbic Acid 4%

Glycerin 3%

Sodium Hyaluronate 2%

Limnanthes Alba (Meadowfoam) Seed Oil 2%

Simmondsia Chinensis (Jojoba) Seed Oil 2%

Purpose

Skin care

Uses

STEP1: Clean and thoroughly dry your skin.

STEP2: Twist the bottom of the product.

STEP3: Gently apply to the skin or other desired areas.

Warning

.For external use only.

Stop use and ask a doctor if

rash occurs.

Do not use

on damaged or broken skin.

When using this product

keep out of eyes. Rinse withwater to remove.

Keep out of reach of children.

If swallowed, get medical help or contact a Poison Control Center right away.

DOSAGE & ADMINISTRATION

Squeeze out an appropriate amount of sunscreen and spread evenly on skin.